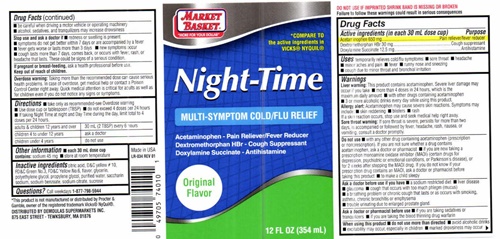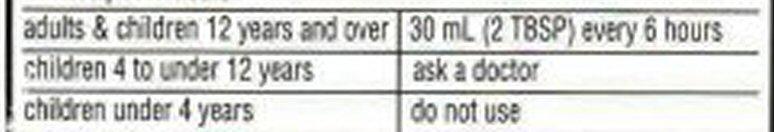 DRUG LABEL: NIGHT-TIME
NDC: 53942-501 | Form: LIQUID
Manufacturer: DeMoulas Market Basket
Category: otc | Type: HUMAN OTC DRUG LABEL
Date: 20231229

ACTIVE INGREDIENTS: ACETAMINOPHEN 650 mg/30 mL; DEXTROMETHORPHAN HYDROBROMIDE 30 mg/30 mL; DOXYLAMINE SUCCINATE 12.5 mg/30 mL
INACTIVE INGREDIENTS: CITRIC ACID MONOHYDRATE; D&C YELLOW NO. 10; FD&C GREEN NO. 3; FD&C YELLOW NO. 6; GLYCERIN; POLYETHYLENE GLYCOL 400; PROPYLENE GLYCOL; WATER; SACCHARIN SODIUM; SODIUM BENZOATE; SODIUM CITRATE; SUCROSE

Night-Time - 501

Drug Facts Active ingredients (in each 30 mL dose cup)

Acetaminophen 650 mg

Dextromethorphan HBr 30 mg

Doxylamine Succinate 12.5 mg

Purpose

Pain reliever/fever reducer
Cough suppressant
Antihistamine

Keep out of reach of children

Uses

temporarily relieves cold/flu symptoms:

- sore throat
- minor aches and pain
- runny nose and sneezing
- cough due to minor sore throat and bronchial irritation
- headache
- fever

Warnings

Liver warning:This product contains acetaminophen. Severe liver damage may occur if you take

- more than 4 doses in 24 hours, which is the maximum daily amount
- with other drugs containing acetaminophen
- 3 or more alcoholic drinks every day while using this product.

Allergy Alert:Acetaminophen may causesevere skin reactions. Symptoms may include:

- skinreddening
- blisters
- rash

If a skin reactions occurs, stop and seek medical help right away.

Sore throat warning: If sore throat is severe, persists for more than 2 days, is accompanied or followed by fever, headache, rash, nausea, or vomiting, consult a doctor promptly.

Do not use

- with any other drug containing acetaminophen (prescription or nonprescription) If you are not sure whether a drug contains acetaminophen, ask a doctor or pharmacist
- if you are now taking a prescription monoamine oxidase inhibitor (MAOI) (certain drugs for depression,psychiatric or emotional conditions, or Parkinson's disease), or for 2 weeks after stopping the MAOI drug. If you do not know if your prescription drug contains an MAOI, ask a doctor or pharmacist before taking this product
- to make a child sleepy

Ask a doctor before use if you have

- a sodium restricted diet
- liver disease
- glaucoma
- cough that occurs with too much phlegm (mucus)
- a breathing problem or chronic cough that lasts or as occurs with smoking, asthma, chronic bronchitis or emphysema
- trouble urinating due to enlarged prostate gland

Ask a doctor or pharmacist before use

- if you are taking sedatives or tranquilizers
- if you are taking the blood thinning drug warfarin

When using this product

- do not use more than directed
- avoid alcoholic drinks
- excitability may occur, especially in children
- marked drowsiness may occur
- be careful when driving a motor vehicle or operating machinery
- alcohol, sedatives, and tranquilizers may increase drowsiness

Stop use and ask a doctor if

- redness or swelling is present
- symptoms do not get better within 7 days or are accompanied by a fever
- fever gets worse or lasts more than 3 days
- new symptoms occur
- cough lasts more than 7 days, comes back, or occurs with fever, rash, headache that lasts

- These could be signs of a serious condition.

If pregnant or breast-feeding

ask a health professional before use.

Overdose warning

Taking more than the recommended dose can cause serious health problems. In case of overdose, get medical help or contact a Poison Control Center right away. Quick medical attention is critical for adults as well as for children even if you do not notice any signs or symptoms.

Directions

- take only as recommended-see Overdose warnings
- Use dose cup or tablespoon (TBSP)
- do not exceed 4 doses per 24 hours
- If taking Night Time at night and Day Time during the day, limit total to 4 doses per 24 hours

Other information

- each 30 mL dose cup contains:
- sodium 45 mg
- store at room temperature

Inactive ingredients

citric acid, D and C yellow No. 10, FD and C Green No. 3, FD and C Yellow No. 6, flavor, glycerin, polyethylene glycol, propylene glycol, purified water, saccharin sodium, sodium benzoate, sodium citrate, sucrose

Questions?

Call weekdays

1-877-798-5944

Market Basket Night-Time product label

MARKET BASKET®

"MORE FOR YOUR DOLLAR"

* COMPARE TO THE ACTIVE INGREDIENTS IN VICKS® NYQUIL®
NIGHT-TIME

MULTI-SYMPTOM COLD/FLU RELIEF
Acetaminophen - Pain Reliever/Fever Reducer
Dextromethorphan HBr - Cough Suppressant
Doxylamine Succinate - Antihistamine

Original Flavor

12 FL OZ (354 mL)
DO NOT USE IF IMPRINTED SHRINK BAND IS MISSING OR BROKEN

Failure to followthese warnings could result in serious complications
*This product is not manufactured or distributed by Proctor & Gamble, distributor of Vicks® Nyquil® LR-002
Made in the USA
DISTRIBUTED BY DEMOULAS SUPERMARKETS INC.

875 EAST STREET - TEWKSBURY, MA 01876

LR - 034 REV 01

res